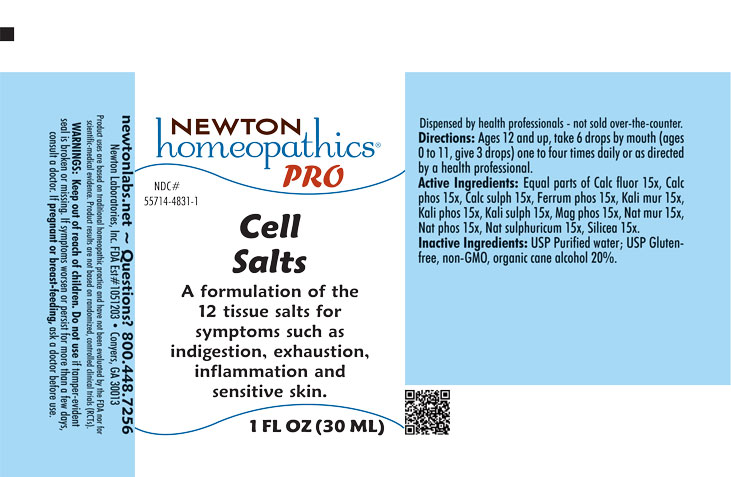 DRUG LABEL: Cell Salts
NDC: 55714-4831 | Form: LIQUID
Manufacturer: Newton Laboratories, Inc.
Category: homeopathic | Type: HUMAN OTC DRUG LABEL
Date: 20250725

ACTIVE INGREDIENTS: CALCIUM FLUORIDE 15 [hp_X]/1 mL; TRIBASIC CALCIUM PHOSPHATE 15 [hp_X]/1 mL; CALCIUM SULFATE ANHYDROUS 15 [hp_X]/1 mL; FERROSOFERRIC PHOSPHATE 15 [hp_X]/1 mL; POTASSIUM CHLORIDE 15 [hp_X]/1 mL; DIBASIC POTASSIUM PHOSPHATE 15 [hp_X]/1 mL; POTASSIUM SULFATE 15 [hp_X]/1 mL; MAGNESIUM PHOSPHATE, DIBASIC TRIHYDRATE 15 [hp_X]/1 mL; SODIUM CHLORIDE 15 [hp_X]/1 mL; SODIUM PHOSPHATE, DIBASIC, HEPTAHYDRATE 15 [hp_X]/1 mL; SODIUM SULFATE 15 [hp_X]/1 mL; SILICON DIOXIDE 15 [hp_X]/1 mL
INACTIVE INGREDIENTS: ALCOHOL; WATER

Cell 4831L

INDICATIONS & USAGE SECTION

A formulation of the 12 tissue salts for symptoms such as indigestion, exhaustion, inflammation and sensitive skin.

DOSAGE & ADMINISTRATION SECTION

Directions: Ages 12 and up, take 6 drops by mouth (ages 0 to 11, take 3 drops) one to four times daily or as directed by a health professional.

WARNINGS SECTION

WARNINGS: Keep out of reach of children. Do not use if tamper-evident seal is broken or missing. If symptoms worsen or persist for more than a few days, consult a doctor. If pregnant or breast-feeding, ask a doctor before use.

QUESTIONS SECTION

newtonlabs.net - Questions? 800 448-7256

Newton Laboratories, Inc. FDA Est # 1051203 - Conyers, GA 30013

OTC - PURPOSE SECTION

A formulation of the 12 tissue salts for symptoms such as indigestion, exhaustion, inflammation and sensitive skin.

OTC - ACTIVE INGREDIENT SECTION

Equal parts of Calc. fluor. 15x, Calc. phos. 15x, Calc.sulph. 15x, Ferrum phos. 15x, Kali mur. 15x, Kali phos. 15x, Kali sulph. 15x, Mag. phos. 15x, Nat. mur. 15x, Nat. phos. 15x, Nat.sulphuricum 15x, Silicea 15x.

OTC - PREGNANCY OR BREAST FEEDING SECTION

If pregnant or breast-feeding, ask a doctor before use.

OTC - KEEP OUT OF REACH OF CHILDREN SECTION

Keep out of reach of children.